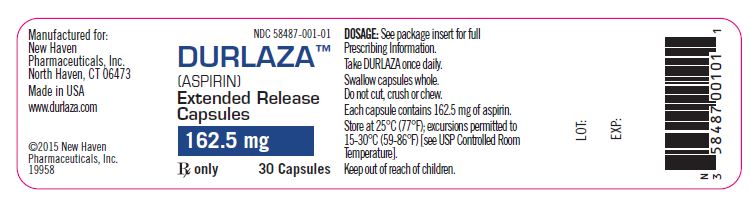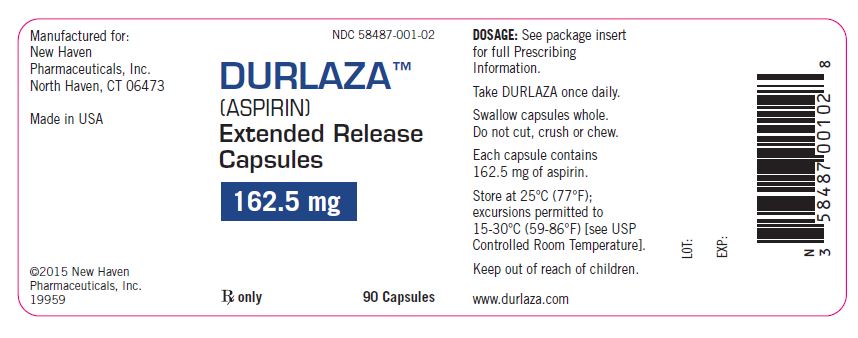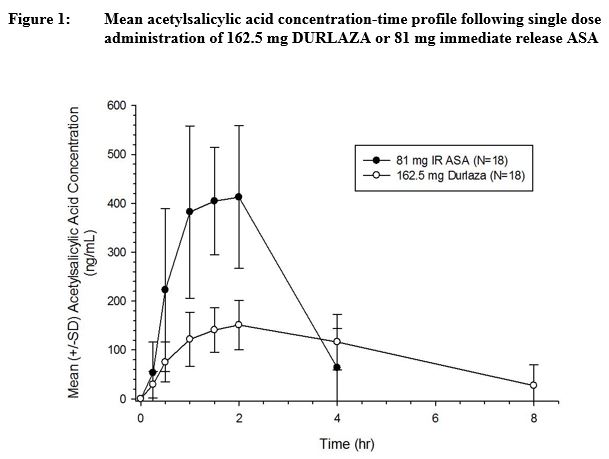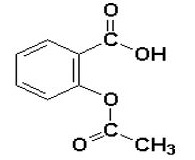 DRUG LABEL: DURLAZA 
NDC: 58487-001 | Form: CAPSULE, EXTENDED RELEASE
Manufacturer: New Haven Pharmaceuticals, Inc.
Category: prescription | Type: HUMAN PRESCRIPTION DRUG LABEL
Date: 20150925

ACTIVE INGREDIENTS: Aspirin 162.5 mg/1 1
INACTIVE INGREDIENTS: Ethylcelluloses; Povidones; Castor Oil; Tartaric Acid; Magnesium Stearate; Silicon Dioxide; Talc; Gelatin; Titanium Dioxide

HIGHLIGHTS OF PRESCRIBING INFORMATION

These highlights do not include all the information needed to use DURLAZA™ safely and effectively. See full prescribing information for DURLAZA.
DURLAZA (aspirin) Extended Release Capsules, for oral use
Initial U.S. Approval:2015

1 INDICATIONS AND USAGE

DURLAZA is a nonsteroidal anti-inflammatory drug indicated to reduce the risk of death and myocardial infarction (MI) in patients with chronic coronary artery disease, such as patients with a history of MI or unstable angina pectoris or with chronic stable angina and to reduce the risk of death and recurrent stroke in patients who have had an ischemic stroke or transient ischemic attack (1)

Limitation of Use: Use immediate-release aspirin, not DURLAZA in situations where a rapid onset of action is required (such as acute treatment of myocardial infarction or before percutaneous coronary intervention). (1, 4)

2 DOSAGE AND ADMINISTRATION

The recommended dose is 162.5 mg per day with a full glass of water at the same time each day (2)

3 DOSAGE FORMS AND STRENGTHS

- Capsules, 162.5 mg (3)

4 CONTRAINDICATIONS

- Hypersensitivity to nonsteroidal anti-inflammatory drug products (4)
- Asthma, rhinitis, and nasal polyps (4)

5 WARNINGS AND PRECAUTIONS

- Increased risk of bleeding. (5.1)
- DURLAZA can cause gastric mucosal irritation and bleeding. Patients with a history of active peptic ulcer disease are at particular risk. (5.2)
- DURLAZA can cause fetal harm when administered to a pregnant woman. (5.3,8.1)

6 ADVERSE REACTIONS

- Most common adverse reactions are Gastrointestinal (6)

To report SUSPECTED ADVERSE REACTIONS, contact New Haven Pharmaceuticals at (877) 824-2483 or www.newhavenpharma.com or FDA at 1-800-FDA-1088 or www.fda.gov/medwatch.

7 DRUG INTERACTIONS

- Alcohol: do not take DURLAZA 2 hours before or 1 hour after consuming alcohol (7)
- Dual inhibition of the renin-angiotensin system: Increased risk of renal impairment, hypotension and hyperkalemia (7)
- Anticoagulant and antiplatelets: increased risk of bleeding (7)
- Anticonvulsants: decreased phenytoin concentration and increased serum valproic acid levels (7)
- Methotrexate: increased risk of bone marrow toxicity (7)
- NSAIDs: Increased risk of bleeding. Nonselective NSAIDs may interfere with DURLAZAs antiplatelet effect (7)

8 USE IN SPECIFIC POPULATIONS

- Pregnancy: Avoid use during the third trimester (8.1)
- Hepatic Impairment: Avoid use in patients with severe impairment (8.6)
- Renal Impairment: Avoid use in patients with GFR less than 10 mL/min (8.7)

FULL PRESCRIBING INFORMATION

1 INDICATIONS AND USAGE

DURLAZA is indicated to:

1. Reduce the risk of death and myocardial infarction (MI) in patients with chronic coronary artery disease, such as patients with a history of MI or unstable angina pectoris or with chronic stable angina
2. Reduce the risk of death and recurrent stroke in patients who have had an ischemic stroke or transient ischemic attack

Limitation of Use: Use immediate-release aspirin, not DURLAZA in situations where a rapid onset of action is required (such as acute treatment of myocardial infarction or before percutaneous coronary intervention).

2 DOSAGE AND ADMINISTRATION

The recommended dose of DURLAZA is one capsule (162.5 mg) once daily. Take the capsules with a full glass of water at the same time each day.

Swallow DURLAZA capsules whole. Do not cut, crush or chew capsules.

Do not take DURLAZA 2 hours before or 1 hour after consuming alcohol [see Warnings and Precautions (5)].

3 DOSAGE FORMS AND STRENGTHS

DURLAZA (aspirin) Extended Release Capsules are supplied as white to off-white opaque capsules each containing 162.5 mg of aspirin.

4 CONTRAINDICATIONS

DURLAZA is contraindicated:

- In patients with a hypersensitivity to nonsteroidal anti-inflammatory drugs (NSAIDs).
- In patients with the syndrome of asthma, rhinitis, and nasal polyps. DURLAZA may cause severe urticaria, angioedema, or bronchospasm.

5 WARNINGS AND PRECAUTIONS

5.1 Risk of Bleeding

DURLAZA increases the risk of bleeding. Risk factors for bleeding include the use of other drugs that increase the risk of bleeding (e.g., anticoagulants, antiplatelet agents, and chronic use of NSAIDs) [see Drug Interactions (7)].

5.2 Peptic Ulcer Disease

DURLAZA may cause gastric ulceration and bleeding. Avoid DURLAZA in patients with active peptic ulcer disease.

5.3 Fetal Toxicity

DURLAZA can cause fetal harm when administered to a pregnant woman. Maternal aspirin use during later stages of pregnancy may cause low birth weight, increased incidence for intracranial hemorrhage in premature infants, stillbirths and neonatal death. Because NSAIDs may cause premature closure of the fetal ductus arteriosus, avoid DURLAZA in the third trimester of pregnancy [see Use in Specific Populations (8.1)].

6 ADVERSE REACTIONS

6.1 Clinical Trials Experience

The following is a list of adverse reactions that have been reported in the literature for products containing low dose aspirin [see Warnings and Precautions (5)].

Central Nervous System: Agitation, cerebral edema, coma, confusion, dizziness, headache, lethargy, seizures.

Fluid and Electrolyte: Hyperkalemia, metabolic acidosis, respiratory alkalosis.

Gastrointestinal: Dyspepsia, hepatic enzyme elevation, hepatitis, Reye's Syndrome.

Renal: Interstitial nephritis, papillary necrosis, proteinuria, renal insufficiency and failure.

7 DRUG INTERACTIONS

Alcohol: Do not take DURLAZA 2 hours before or 1 hour after consuming alcohol. Alcohol can interfere with the controlled release properties of DURLAZA.

Renin-angiotensin system (RAS) inhibitors: In patients who are elderly, volume-depleted (including those on diuretic therapy), or who have compromised renal function, coadministration of NSAIDs, including DURLAZA, with RAS inhibitors may result in deterioration of renal function, including possible acute renal failure. These effects are usually reversible. Monitor renal function periodically in patients receiving RAS inhibitors and DURLAZA.

NSAIDs, including DURLAZA may attenuate the antihypertensive effects of RAS inhibitors.

Anticoagulant and antiplatelets: Increased risk of bleeding

Anticonvulsants: Salicylate can displace protein-bound phenytoin and valproic acid, leading to a decrease in the total concentration of phenytoin and an increase in serum valproic acid levels.

Methotrexate: Salicylate can inhibit renal clearance of methotrexate, leading to bone marrow toxicity, especially in the elderly or renal impaired.

Nonsteroidal Anti-inflammatory Drugs (NSAIDs): The concurrent use of DURLAZA with other NSAIDs increases the risk of bleeding and may result in renal impairment.

Ibuprofen can interfere with the anti-platelet effect of low dose aspirin. Patients who use DURLAZA and take a single dose of ibuprofen 400 mg should dose the ibuprofen at least 2-4 hours or longer after ingestion of DURLAZA. Wait 8 hours after ibuprofen dosing, before giving aspirin, to avoid significant interference.

Nonselective NSAIDs may interfere with the antiplatelet effect of low-dose aspirin.

8 USE IN SPECIFIC POPULATIONS

8.1 Pregnancy

Avoid use during the third trimester of pregnancy because NSAIDs such as DURLAZA may cause premature closure of the fetal ductus arteriosus. Salicylate products have also been associated with alterations in maternal and neonatal hemostasis mechanisms, decreased birth weight, and with perinatal mortality.

8.2 Labor and Delivery

Avoid DURLAZA 1 week prior to and during labor and delivery because it can result in excessive blood loss at delivery. Prolonged gestation and prolonged labor due to prostaglandin inhibition have been reported.

8.3 Nursing Mothers

Because of the potential for serious adverse reactions in nursing infants from DURLAZA, choose either to discontinue DURLAZA or discontinue nursing.

8.4 Pediatric Use

Safety and effectiveness in pediatric patients have not been established.

8.5 Geriatric Use

In a large collaborative overview of aspirin for vascular event prevention, including over 14000 patients over 65 years of age, no overall differences in safety or effectiveness were observed between these subjects and younger subjects, and other reported clinical experience has not identified differences in responses between the elderly and younger patients.

8.6 Hepatic Impairment

Avoid DURLAZA in patients with severe hepatic insufficiency.

8.7 Renal Impairment

Avoid DURLAZA in patients with severe renal failure (glomerular filtration rate less than 10 mL/minute).

10 OVERDOSAGE

Salicylate toxicity may result from acute ingestion (overdose) or chronic intoxication. The early signs of salicylic overdose (salicylism), including tinnitus (ringing in the ears), occur at plasma concentrations approaching 200 mcg/mL. Plasma concentrations of aspirin above 300 mcg/mL are clearly toxic. Severe toxic effects are associated with levels above 400 mcg/mL [see Clinical Pharmacology (12.3)]. A single lethal dose of aspirin in adults is not known with certainty but death may be expected at 30 g. For real or suspected overdose, contact a Poison Control Center immediately.

Signs and Symptoms: In acute overdose, severe acid-base and electrolyte disturbances may occur and are complicated by hyperthermia and dehydration. Respiratory alkalosis occurs early while hyperventilation is present, but is quickly followed by metabolic acidosis.

Treatment: Treatment consists primarily of supporting vital functions, increasing salicylate elimination, and correcting the acid-base disturbance. Gastric emptying or lavage is recommended as soon as possible after ingestion, even if the patient has vomited spontaneously. After lavage or emesis, administer activated charcoal, as a slurry, if less than 3 hours have passed since ingestion.

Severity of aspirin intoxication is determined by measuring the blood salicylate level. Monitor acid-base status with serial blood gas and serum pH measurements. Maintain fluid and electrolyte balance.

In severe cases, hyperthermia and hypovolemia are the major immediate threats to life. Replace fluid intravenously and correct acidosis. Monitor plasma electrolytes and pH to promote alkaline diuresis of salicylate if renal function is normal. Glucose may be required to control hypoglycemia.

Hemodialysis and peritoneal dialysis can reduce the body aspirin content. In patients with renal insufficiency or in cases of life-threatening intoxication, dialysis is usually required. Exchange transfusion may be indicated in infants and young children.

11 DESCRIPTION

DURLAZA Capsules contain aspirin, which is a platelet aggregation inhibitor, for oral administration. Chemically, aspirin is acetylsalicylic acid. It has the following structural formula:

Aspirin is white or almost white crystalline powder or colorless crystals consisting of cubical and squared crystals. It is slightly soluble in water, and soluble in ethanol. When exposed to moisture, aspirin hydrolyzes into salicylic and acetic acids, and gives off a vinegary odor. It has a molecular weight of 180.16 g/mole and a molecular formula C9H8O4.

Durlaza capsules also include the following inactive ingredients: ethylcellulose, povidone, castor oil, tartaric acid, magnesium stearate, colloidal anhydrous silica, and talc.

The capsule shell contains gelatin and titanium dioxide.

12 CLINICAL PHARMACOLOGY

12.1 Mechanism of Action

Aspirin [acetylsalicylic acid (ASA)] inhibits prostaglandin synthesis resulting in inhibition of platelet aggregation for their lifespan of about 7-10 days. The acetyl group of aspirin binds with a serine residue of cyclooxygenase-1 (COX-1), resulting in irreversible inactivation of the enzyme. Inhibition of COX-1 prevents conversion of arachidonic acid to thromboxane A2 (TXA2), which is a potent agonist of platelet aggregation.

12.2 Pharmacodynamics

The dose-response relationship for DURLAZA and immediate release (IR) aspirin towards COX-1 inhibition was characterized by examining the inhibition of serum TXB2 and urine 11-dehydro-TXB2 at 24 h following a single dose. Doses over the range of 20 mg to 325 mg for DURLAZA and 5 mg to 81 mg for IR aspirin respectively were studied. Half-maximal inhibition of serum TXB2 and urine 11-dehydro-TXB2 occurred with doses of DURLAZA (ID50) about 2-fold the dose of immediate release (IR) aspirin. Based on this relationship, the pharmacodynamic effect of DURLAZA 162.5 mg is similar to that attained with IR aspirin 81 mg. The mean inhibition of serum TXB2 following DURLAZA (82%) is lower when compared to IR aspirin 81 mg (93%) following the first dose. However, upon repeat administration, near maximal inhibition of serum TXB2 is achieved, similar to what is achieved following repeated daily doses of IR aspirin.

12.3 Pharmacokinetics

Following oral administration, DURLAZA exhibits extended release of aspirin from the encapsulated microparticles, thereby prolonging the absorption of aspirin across the GI tract compared to IR aspirin (Figure 1). Once absorbed, aspirin is metabolized, distributed, and excreted in a manner similar to that of aspirin absorbed from IR dosage forms.

Absorption: Following administration of DURLAZA, the time to reach peak plasma concentration of aspirin is slightly longer compared to following IR aspirin dosage form. Median Tmax for DURLAZA is about 2 h when compared to 1 h following IR aspirin (see Figure 1). The mean Cmax for DURLAZA is approximately 35% of that following IR aspirin 81 mg. The area under the plasma concentration-time curve for aspirin following administration of DURLAZA is approximately 70% of that following IR aspirin. The rate of DURLAZA absorption is dependent on food, alcohol, and gastric pH.

Distribution: The volume of distribution of usual doses of aspirin in normal subjects averages approximately 170 mL/kg of body weight.

Metabolism: Aspirin is rapidly hydrolyzed in the plasma to salicylic acid such that plasma levels of aspirin following DURLAZA administration are essentially undetectable 4-8 hours after dosing. In contrast to immediate release aspirin, measurable levels of salicylic acid at 24 hours following a single dose of DURLAZA were observed. Salicylic acid is primarily conjugated in the liver to form salicyluric acid, a phenolic glucuronide, an acyl glucuronide, and a number of minor metabolites.

Elimination: The mean plasma half-life of aspirin may range from 20 to 60 min. Following therapeutic doses, approximately 10% is found excreted in the urine as salicylic acid, 75% as salicylic acid, and 10% phenolic and 5% acyl glucuronides of salicylic acid.

13 NONCLINICAL TOXICOLOGY

13.1 Carcinogenesis, Mutagenesis, Impairment of Fertility

No carcinogenesis, mutagenesis or impairment of fertility studies were conducted with DURLAZA. Aspirin is not considered to be genotoxic or carcinogenic. Studies with oral aspirin in pregnant rats demonstrated the occurrence of fetal malformations at oral doses at or above 250 mg/kg [Human equivalent dose (HED) 40 mg/kg].

13.2 Animal Toxicology and/or Pharmacology

A single oral dose of 2500 mg/kg (HED 405 mg/kg) DURLAZA was well-tolerated in the gastrointestinal tract of the rat whereas a single oral dose of IR aspirin ≥740 mg/kg (HED 120 mg/kg) caused lethality and gastric mucosal damage.

14 CLINICAL STUDIES

14.1 Chronic Coronary Artery Disease

This indication is supported by the results of six large, randomized, multi-center, placebo controlled trials of predominantly male post-MI subjects and one randomized placebo-controlled study of men with unstable angina pectoris. Aspirin therapy in MI subjects gave about 20% reduction in the relative risk of the combined endpoint of death or nonfatal reinfarction. In the study of male unstable angina patients, aspirin reduced the event rate from 10% in the placebo patients to 5% in the patients treated with aspirin.

It is also supported by a randomized, multi-center, double-blind trial designed to assess the effect of aspirin in reducing the risk of MI in patients with chronic stable angina pectoris. Aspirin reduced the relative risk of the primary combined endpoint of nonfatal MI, fatal MI, and sudden death by 34%. The secondary endpoint for vascular events (the first occurrence of MI, stroke, or vascular death) was also significantly reduced.

14.2 Ischemic Stroke and Transient Ischemic Attack (TIA)

In clinical trials of subjects with ischemic stroke or TIAs, aspirin has been shown to reduce the relative risk of the combined endpoint of stroke or death and the combined endpoint of TIA, stroke, or death by about 13 - 18%.

16 HOW SUPPLIED/STORAGE AND HANDLING

DURLAZA Capsules, 162.5 mg, are supplied as follows:

Size 2 white to off-white opaque capsules imprinted with the name Durlaza

Bottles of 30 capsules NDC 58487-001-01

Bottles of 90 capsules NDC 58487-001-02

Special Precautions for Storage: Store at 25 °C (77 °F); excursions permitted to 15 - 30°C (59 -86°F) [see USP Controlled Room Temperature].

17 PATIENT COUNSELING INFORMATION

Discuss the following with patients prior to initiating treatment with DURLAZA and periodically during the course of ongoing treatment:

Bleeding

- Inform patients that they may bruise or bleed more easily or that it may take longer to stop bleeding and to report to their physician any prolonged, unusual or excessive bleeding. Inform patients to notify their physician about blood in their stool or urine and the signs and symptoms of occult bleeding [see Warnings and Precautions (5)].
- Inform patients about the signs and symptoms of GI side effects and seek medical advice when experiencing any of these signs and symptoms [see Warnings and Precautions (5)].

Hypersensitivity

- Advise the patient to discontinue DURLAZA and seek immediate medical attention if any signs or symptoms of a hypersensitivity reaction occur [see Contraindications (4)].

Alcohol Consumption

- Inform patients they should not take DURLAZA 2 hours before or 1 hour after consuming alcohol. Counsel patients who drink three or more alcoholic drinks every day about the risk of bleeding involved in chronic, heavy alcohol use while taking DURLAZA [see Warnings and Precautions (5)].

Administration Instructions

- Advise patients to swallow DURLAZA capsules whole and not to chew or crush them.
- Remind patients not to discontinue DURLAZA without first notifying and discussing with their physician. Advise patients not to use extra medicine to make up a missed dose.
- Advise patients not to take ibuprofen around the same time as DURLAZA [see Drug Interactions (7)].

Pregnancy and Lactation

- Advise patients that ASA containing products such as DURLAZA cause harm to fetuses especially during the third trimester of pregnancy. Inform patients to notify their physician if they are pregnant, plan to become pregnant, breastfeed or are considering breastfeeding prior or during receiving treatment with DURLAZA [See Use in Special Populations (8.2, 8.3)].

Manufactured for New Haven Pharmaceuticals, Inc.
North Haven, CT 06473
DURLAZA Capsules manufactured in USA
Distributed by Cardinal Health 105, Inc.

PACKAGE LABEL

NDC 58487-001-02
DURLAZA™
(ASPIRIN)
Extended Release Capsules
162.5 mg
Rx Only
90 Capsules
DOSAGE: See package insert for full Prescribing Information.
Take DURLAZA once daily.
Swallow capsules whole.
Do not cut, crush or chew.
Each capsule contains 162.5 mg of aspirin.
Store at 25°C (77°F); excursions permitted to 15-30°C (59-86°F) [see USP Controlled Room Temperature].
Keep out of reach of children.
www.durlaza.com
Manufactured for:
New Haven Pharmaceuticals, Inc.
North Haven, CT 06473
Made in USA
©2015 New Haven Pharmaceuticals, Inc.
19959
LOT:
EXP:

PACKAGE LABEL

NDC 58487-001-01
DURLAZA™
(ASPIRIN)
Extended Release Capsules
162.5 mg
Rx Only
30 Capsules
DOSAGE: See package insert for full Prescribing Information.
Take DURLAZA once daily.
Swallow capsules whole.
Do not cut, crush or chew.
Each capsule contains 162.5 mg of aspirin.
Store at 25°C (77°F); excursions permitted to 15-30°C (59-86°F) [see USP Controlled Room Temperature].
Keep out of reach of children.
Manufactured for:
New Haven Pharmaceuticals, Inc.
North Haven, CT 06473
Made in USA
www.durlaza.com
©2015 New Haven Pharmaceuticals, Inc.
19958
LOT:
EXP: